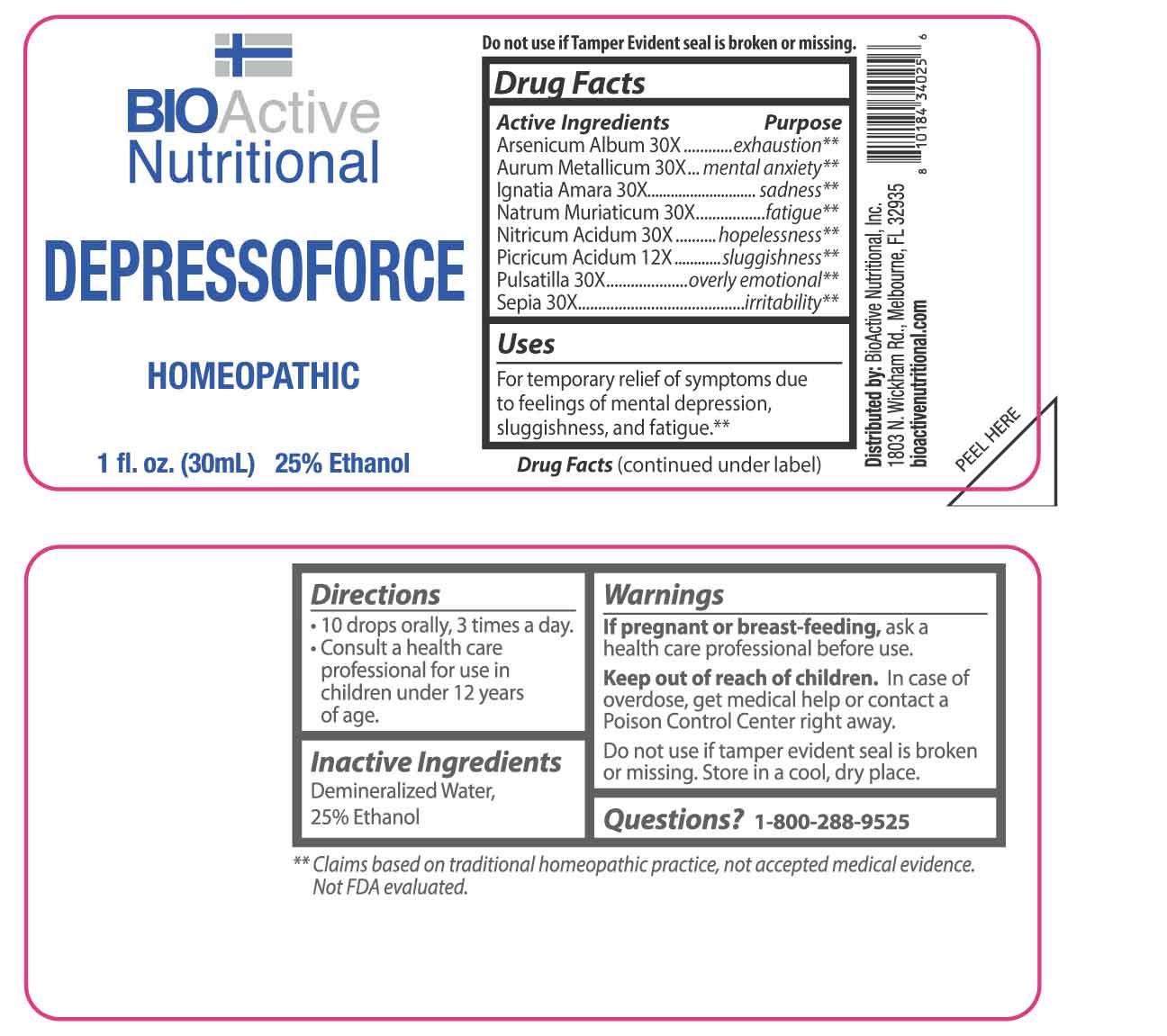 DRUG LABEL: Depressoforce
NDC: 43857-0538 | Form: LIQUID
Manufacturer: BioActive Nutritional, Inc.
Category: homeopathic | Type: HUMAN OTC DRUG LABEL
Date: 20250625

ACTIVE INGREDIENTS: PICRIC ACID 12 [hp_X]/1 mL; ARSENIC TRIOXIDE 30 [hp_X]/1 mL; GOLD 30 [hp_X]/1 mL; STRYCHNOS IGNATII SEED 30 [hp_X]/1 mL; SODIUM CHLORIDE 30 [hp_X]/1 mL; NITRIC ACID 30 [hp_X]/1 mL; PULSATILLA PRATENSIS WHOLE 30 [hp_X]/1 mL; SEPIA OFFICINALIS JUICE 30 [hp_X]/1 mL
INACTIVE INGREDIENTS: WATER; ALCOHOL

DRUG FACTS:

ACTIVE INGREDIENTS:

Arsenicum Album 30X, Aurum Metallicum 30X, Ignatia Amara 30X, Natrum Muriaticum 30X, Nitricum Acidum 30X, Picricum Acidum 12X, Pulsatilla 30X, Sepia 30X.

PURPOSE:

Arsenicum Album - exhaustion,** Aurum Metallicum – mental anxiety,** Ignatia Amara - sadness,** Natrum Muriaticum - fatigue,** Nitricum Acidum - hopelessness,** Picricum Acidum - sluggishness,** Pulsatilla – overly emotional,** Sepia – irritability**

**Claims based on traditional homeopathic practice, not accepted medical evidence. Not FDA evaluated.

USES:

For temporary relief of symptoms due to feelings of mental depression, sluggishness, and fatigue.**

**Claims based on traditional homeopathic practice, not accepted medical evidence. Not FDA evaluated.

WARNINGS:

If pregnant or breast-feeding, ask a health care professional before use.

Keep out of reach of children. In case of overdose, get medical help or contact a Poison Control Center right away.

Do not use if tamper evident seal is broken or missing.

Store in a cool, dry place.

KEEP OUT OF REACH OF CHILDREN:

In case of overdose, get medical help or contact a Poison Control Center right away.

DIRECTIONS:

• 10 drops orally, 3 times a day.

• Consult a health care professional for use in children under 12 years of age.

INACTIVE INGREDIENTS:

Demineralized Water, 25% Ethanol

QUESTIONS:

Distributed by:

BioActive Nutritional, Inc.
1803 N. Wickham Rd.
Melbourne, FL 32935
bioactivenutritional.com

1-800-288-9525

PACKAGE LABEL DISPLAY:

BIOActive Nutritional

DEPRESSOFORCE

HOMEOPATHIC

1 fl. oz. (30mL)